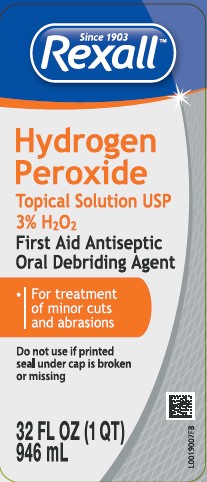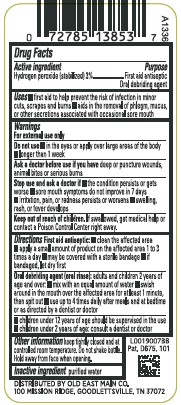 DRUG LABEL: Hydrogen Peroxide
NDC: 55910-871 | Form: SOLUTION
Manufacturer: Old East Main Co.
Category: otc | Type: HUMAN OTC DRUG LABEL
Date: 20260302

ACTIVE INGREDIENTS: HYDROGEN PEROXIDE 30 mg/1 mL
INACTIVE INGREDIENTS: WATER

Rexall 871.001/871AA
3% Hydrogen Peroxide

Active ingredient

Hydrogen peroxide (stabilized) 3%

Purpose

First aid antiseptic

Oral debriding agent

Uses

- first aid to help prevent the risk of infection in minor cuts, scrapes and burns
- aids in the removal of phlegm, mucous or other secretions associated with occasional sore mouth

Warnings

For external use only

Do not use

- in the eyes or apply over large areas of the body
- longer than 1 week

As a doctor before use if you have

deep or puncture wounds, animal bites or serious burns

Stop use and ask a doctor if

- the condition persists or gets worse
- sore mouth symptoms do not improve in 7 days
- irritation, pain or redness persists or worsens
- swelling, rash or fever develops

Keep out of reach of children.

If swallowed, get medical help or contact a Poison Control Center right away.

Directions

First aid antiseptic:

- clean the affected area
- apply a small amount of product on the affected area 1 to 3 times a day
- may be covered with a sterile bandage
- if bandaged, let dry first

Oral debriding agent (oral rinse): adults and children 2 years of age and over:

- mix with an equal amount of water
- swish around in the mouth over the affected area for at least 1 minute and then spit out
- use up to 4 times daily after meals and at bedtime or as directed by a dentist or doctor

- children under 12 years of age should be supervised in the use
- children under 2 years of age: consult a dentist or doctor

Other information

keep tightly closed and at controlled room temperature. Do not shake bottle. Hold away from face when opening.

Inactive ingredient

purified water

adverse reactions

Distributed by: Old East Main Co.

100 MISSION RIDGE GOODLETTSVILLE, TN 37072

Pat. D675, 101

principal display panel

Since 1903

Rexall™

Hydrogen Peroxide

Topical Solution USP

3% H202

First Aid Antiseptic

Oral Debriding Agent

- For treatment of minor cuts and abrasions

Do not use if printed seal under cap is broken or missing

32 FL OZ (1 QT) 946 mL